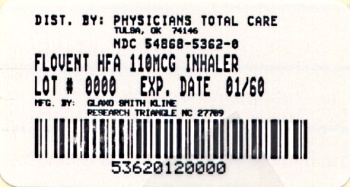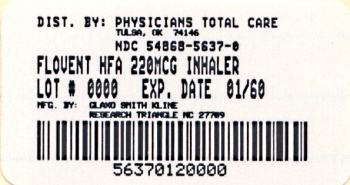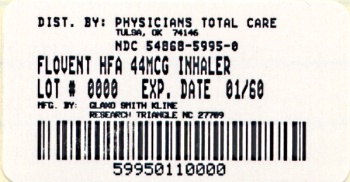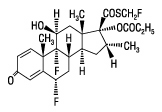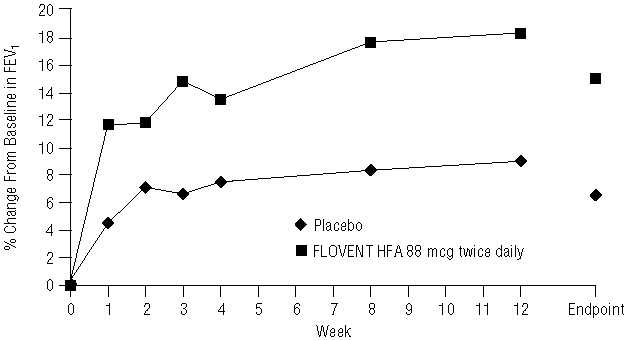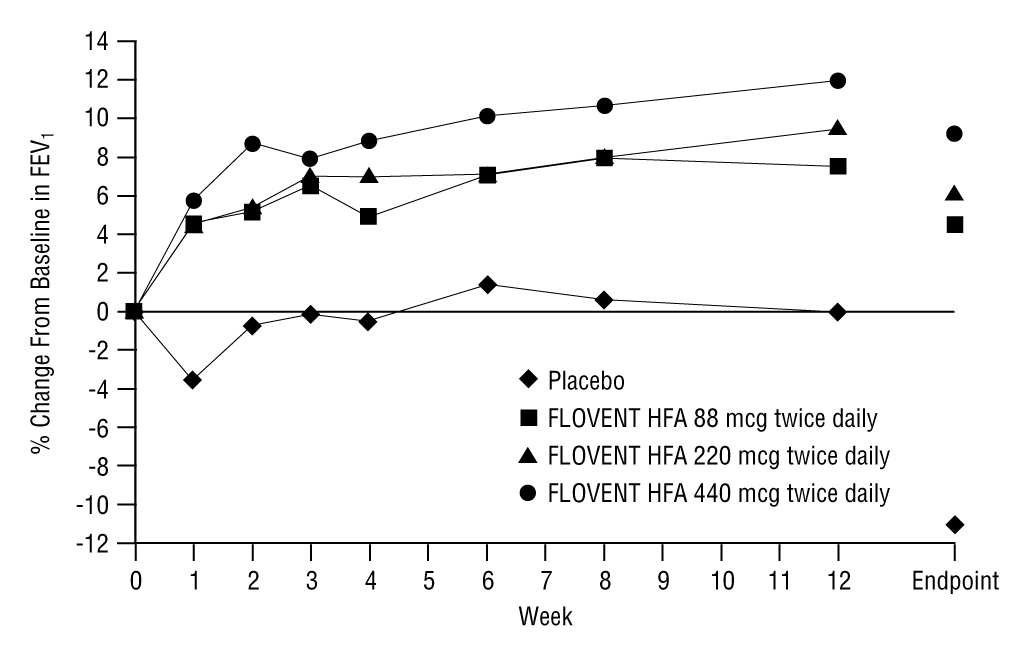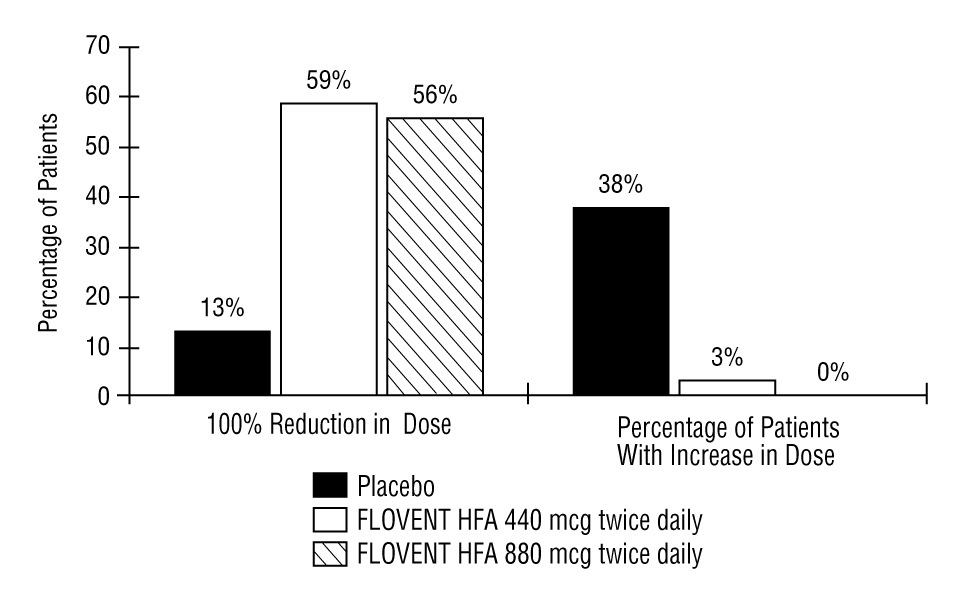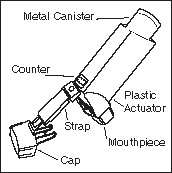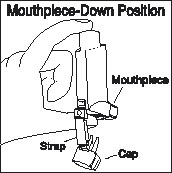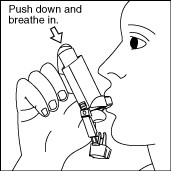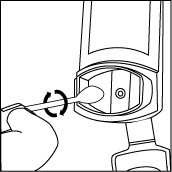 DRUG LABEL: FLOVENT
NDC: 54868-5995 | Form: AEROSOL, METERED
Manufacturer: Physicians Total Care, Inc.
Category: prescription | Type: HUMAN PRESCRIPTION DRUG LABEL
Date: 20120116

ACTIVE INGREDIENTS: FLUTICASONE PROPIONATE 44 ug/1 1
INACTIVE INGREDIENTS: NORFLURANE

HIGHLIGHTS OF PRESCRIBING INFORMATION

These highlights do not include all the information needed to use FLOVENT HFA safely and effectively. See full prescribing information for FLOVENT HFA.
FLOVENT HFA 44 mcg (fluticasone propionate 44 mcg) Inhalation Aerosol
FLOVENT HFA 110 mcg (fluticasone propionate 110 mcg) Inhalation Aerosol
FLOVENT HFA 220 mcg (fluticasone propionate 220 mcg) Inhalation Aerosol
FOR ORAL INHALATION ONLY
Initial U.S. Approval: 1994

1 INDICATIONS AND USAGE

FLOVENT HFA is an inhaled corticosteroid indicated for:

- Maintenance treatment of asthma as prophylactic therapy in patients aged 4 years and older. (1)
- Treatment of asthma for patients requiring oral corticosteroid therapy. (1)

FLOVENT HFA is NOT indicated for the relief of acute bronchospasm. (1)

2 DOSAGE AND ADMINISTRATION

For oral inhalation only. Dosing is based on prior asthma therapy. (2)

Previous Therapy | Recommended Starting Dosage | Highest Recommended Dosage
Patients aged ≥12 years
Bronchodilators alone | 88 mcg twice daily | 440 mcg twice daily
Inhaled corticosteroids | 88-220 mcg twice daily | 440 mcg twice daily
Oral corticosteroids | 440 mcg twice daily | 880 mcg twice daily
Patients aged 4-11 years | 88 mcg twice daily | 88 mcg twice daily

3 DOSAGE FORMS AND STRENGTHS

Inhalation aerosol with 44, 110, or 220 mcg per actuation. (3)

4 CONTRAINDICATIONS

- Primary treatment of status asthmaticus or acute episodes of asthma requiring intensive measures. (4)
- Hypersensitivity to any ingredient. (4)

5 WARNINGS AND PRECAUTIONS

- Localized infections: Candida albicans infection of the mouth and pharynx. Monitor patients periodically for signs of adverse effects on the oral cavity. Advise patients to rinse mouth following inhalation. (5.1)
- Immunosuppression: Potential worsening of existing tuberculosis; fungal, bacterial, viral, or parasitic infection; or ocular herpes simplex. More serious or even fatal course of chickenpox or measles in susceptible patients. Use caution in patients with above because of the potential for worsening of these infections. (5.3)
- Transferring patients from systemic corticosteroids: Risk of impaired adrenal function when transferring from oral steroids. Taper patients slowly from systemic corticosteroids if transferring to FLOVENT HFA. (5.4)
- Hypercorticism and adrenal suppression: May occur with very high dosages or at the regular dosage in susceptible individuals. If such changes occur, discontinue FLOVENT HFA slowly. (5.5)
- Hypersensitivity reactions, including anaphylaxis, may occur after administration of FLOVENT HFA. Discontinue FLOVENT HFA if such reactions occur. (4, 5.6)
- Decreases in bone mineral density: Assess bone mineral density initially and periodically thereafter in patients at risk. (5.7)
- Effect on growth: Monitor growth of pediatric patients. (5.8)
- Glaucoma and cataracts: Close monitoring is warranted. (5.9)

6 ADVERSE REACTIONS

Most common adverse reactions (incidence >3%) include upper respiratory tract infection or inflammation, throat irritation, sinusitis, dysphonia, candidiasis, cough, bronchitis, and headache. (6.1)

To report SUSPECTED ADVERSE REACTIONS, contact GlaxoSmithKline at 1-888-825-5249 or FDA at 1-800-FDA-1088 or www.fda.gov/medwatch

7 DRUG INTERACTIONS

Use with strong cytochrome P450 3A4 inhibitors such as ritonavir and ketoconazole is not recommended. Systemic corticosteroid effects may occur. (7.1)

8 USE IN SPECIFIC POPULATIONS

Hepatic impairment: Monitor patients for signs of increased drug exposure. (8.6)

FULL PRESCRIBING INFORMATION

1 INDICATIONS AND USAGE

FLOVENT® HFA Inhalation Aerosol is indicated for the maintenance treatment of asthma as prophylactic therapy in patients aged 4 years and older. It is also indicated for patients requiring oral corticosteroid therapy for asthma. Many of these patients may be able to reduce or eliminate their requirement for oral corticosteroids over time.

FLOVENT HFA Inhalation Aerosol is NOT indicated for the relief of acute bronchospasm.

2 DOSAGE AND ADMINISTRATION

FLOVENT HFA should be administered by the orally inhaled route only in patients aged 4 years and older. Individual patients will experience a variable time to onset and degree of symptom relief. Maximum benefit may not be achieved for 1 to 2 weeks or longer after starting treatment.

After asthma stability has been achieved, it is always desirable to titrate to the lowest effective dosage to reduce the possibility of side effects. For patients who do not respond adequately to the starting dosage after 2 weeks of therapy, higher dosages may provide additional asthma control. The safety and efficacy of FLOVENT HFA when administered in excess of recommended dosages have not been established.

The recommended starting dosage and the highest recommended dosage of FLOVENT HFA, based on prior asthma therapy, are listed in Table 1.

Table 1. Recommended Dosages of FLOVENT HFA Inhalation Aerosol
NOTE: In all patients, it is desirable to titrate to the lowest effective dosage once asthma stability is achieved.
Previous Therapy | Recommended Starting Dosage | Highest Recommended Dosage
Adult and adolescent patients (aged ≥12 years) | 88 mcg twice daily; 88-220 mcg twice dailya; 440 mcg twice daily | 440 mcg twice daily; 440 mcg twice daily; 880 mcg twice daily
Bronchodilators alone; Inhaled corticosteroids; Oral corticosteroidsb | 88 mcg twice daily; 88-220 mcg twice dailya; 440 mcg twice daily | 440 mcg twice daily; 440 mcg twice daily; 880 mcg twice daily
Pediatric patients (aged 4-11 years)c | 88 mcg twice daily | 88 mcg twice daily

a Starting dosages above 88 mcg twice daily may be considered for patients with poorer asthma control or those who have previously required doses of inhaled corticosteroids that are in the higher range for the specific agent.

b For patients currently receiving chronic oral corticosteroid therapy, prednisone should be reduced no faster than 2.5 to 5 mg/day on a weekly basis beginning after at least 1 week of therapy with FLOVENT HFA. Patients should be carefully monitored for signs of asthma instability, including serial objective measures of airflow, and for signs of adrenal insufficiency [see Warnings and Precautions (5.4)]. Once prednisone reduction is complete, the dosage of FLOVENT HFA should be reduced to the lowest effective dosage.

c Recommended pediatric dosage is 88 mcg twice daily regardless of prior therapy. A valved holding chamber and face mask may be used to deliver FLOVENT HFA to young patients.

FLOVENT HFA should be primed before using for the first time by releasing 4 test sprays into the air away from the face, shaking well for 5 seconds before each spray. In cases where the inhaler has not been used for more than 7 days or when it has been dropped, prime the inhaler again by shaking well for 5 seconds and releasing 1 test spray into the air away from the face.

3 DOSAGE FORMS AND STRENGTHS

FLOVENT HFA is an inhalation aerosol. Each actuation delivers 44, 110, or 220 mcg of fluticasone propionate from the actuator. FLOVENT HFA 44 mcg is supplied in 10.6-g pressurized aluminum canisters, and FLOVENT HFA 110 mcg and FLOVENT HFA 220 mcg are supplied in 12-g pressurized aluminum canisters. Each canister contains 120 metered inhalations and is fitted with a counter and a dark orange oral actuator with a peach strapcap.

4 CONTRAINDICATIONS

The use of FLOVENT HFA is contraindicated in the following conditions:

- Primary treatment of status asthmaticus or other acute episodes of asthma where intensive measures are required [see Warnings and Precautions (5.2)]
- Hypersensitivity to any of the ingredients of FLOVENT HFA contraindicates their use [see Warnings and Precautions (5.6), Adverse Reactions (6.2), Description (11)]

5 WARNINGS AND PRECAUTIONS

5.1 Local Effects

In clinical studies, the development of localized infections of the mouth and pharynx with Candida albicans has occurred in patients treated with FLOVENT HFA. When such an infection develops, it should be treated with appropriate local or systemic (i.e., oral antifungal) therapy while treatment with FLOVENT HFA continues, but at times therapy with FLOVENT HFA may need to be interrupted. Patients should rinse the mouth after inhalation of FLOVENT HFA [see Adverse Reactions (6.1)].

5.2 Acute Asthma Episodes

FLOVENT HFA is not to be regarded as a bronchodilator and is not indicated for rapid relief of bronchospasm. Patients should be instructed to contact their physicians immediately when episodes of asthma that are not responsive to bronchodilators occur during the course of treatment with FLOVENT HFA. During such episodes, patients may require therapy with oral corticosteroids.

5.3 Immunosuppression

Persons who are using drugs that suppress the immune system are more susceptible to infections than healthy individuals. Chickenpox and measles, for example, can have a more serious or even fatal course in susceptible children or adults using corticosteroids. In such children or adults who have not had these diseases or been properly immunized, particular care should be taken to avoid exposure. How the dose, route, and duration of corticosteroid administration affect the risk of developing a disseminated infection is not known. The contribution of the underlying disease and/or prior corticosteroid treatment to the risk is also not known. If a patient is exposed to chickenpox, prophylaxis with varicella zoster immune globulin (VZIG) may be indicated. If a patient is exposed to measles, prophylaxis with pooled intramuscular immunoglobulin (IG) may be indicated. (See the respective package inserts for complete VZIG and IG prescribing information.) If chickenpox develops, treatment with antiviral agents may be considered.

Because of the potential for worsening infections, inhaled corticosteroids should be used with caution, if at all, in patients with active or quiescent tuberculosis infection of the respiratory tract; untreated systemic fungal, bacterial, viral, or parasitic infections; or ocular herpes simplex.

5.4 Transferring Patients From Systemic Corticosteroid Therapy

Particular care is needed for patients who have been transferred from systemically active corticosteroids to inhaled corticosteroids because deaths due to adrenal insufficiency have occurred in patients with asthma during and after transfer from systemic corticosteroids to less systemically available inhaled corticosteroids. After withdrawal from systemic corticosteroids, a number of months are required for recovery of hypothalamic-pituitary-adrenal (HPA) function.

Patients requiring oral corticosteroids should be weaned slowly from systemic corticosteroid use after transferring to FLOVENT HFA. In a clinical trial of 168 patients, prednisone reduction was successfully accomplished by reducing the daily prednisone dose on a weekly basis following initiation of treatment with FLOVENT HFA. Successive reduction of prednisone dose was allowed only when lung function, symptoms, and as-needed short-acting beta-agonist use were better than or comparable to that seen before initiation of prednisone dose reduction. Lung function (forced expiratory volume in 1 second [FEV1] or morning peak expiratory flow [AM PEF]), beta-agonist use, and asthma symptoms should be carefully monitored during withdrawal of oral corticosteroids. In addition to monitoring asthma signs and symptoms, patients should be observed for signs and symptoms of adrenal insufficiency such as fatigue, lassitude, weakness, nausea and vomiting, and hypotension.

Patients who have been previously maintained on 20 mg or more per day of prednisone (or its equivalent) may be most susceptible, particularly when their systemic corticosteroids have been almost completely withdrawn. During this period of HPA suppression, patients may exhibit signs and symptoms of adrenal insufficiency when exposed to trauma, surgery, or infection (particularly gastroenteritis) or other conditions associated with severe electrolyte loss. Although inhaled corticosteroids may provide control of asthma symptoms during these episodes, in recommended doses they supply less than normal physiological amounts of glucocorticoid (cortisol) systemically and do NOT provide the mineralocorticoid activity that is necessary for coping with these emergencies.

During periods of stress or a severe asthma attack, patients who have been withdrawn from systemic corticosteroids should be instructed to resume oral corticosteroids immediately and to contact their physicians for further instruction. These patients should also be instructed to carry a warning card indicating that they may need supplementary systemic corticosteroids during periods of stress or a severe asthma attack.

Transfer of patients from systemic corticosteroid therapy to FLOVENT HFA may unmask conditions previously suppressed by the systemic corticosteroid therapy (e.g., rhinitis, conjunctivitis, eczema, arthritis, eosinophilic conditions). Some patients may experience symptoms of systemically active corticosteroid withdrawal (e.g., joint and/or muscular pain, lassitude, and depression, despite maintenance or even improvement of respiratory function).

5.5 Hypercorticism and Adrenal Suppression

Fluticasone propionate will often help control asthma symptoms with less suppression of HPA function than therapeutically equivalent oral doses of prednisone. Since fluticasone propionate is absorbed into the circulation and can be systemically active at higher doses, the beneficial effects of FLOVENT HFA in minimizing HPA dysfunction may be expected only when recommended dosages are not exceeded and individual patients are titrated to the lowest effective dose. A relationship between plasma levels of fluticasone propionate and inhibitory effects on stimulated cortisol production has been shown after 4 weeks of treatment with fluticasone propionate. Since individual sensitivity to effects on cortisol production exists, physicians should consider this information when prescribing FLOVENT HFA.

Because of the possibility of systemic absorption of inhaled corticosteroids, patients treated with FLOVENT HFA should be observed carefully for any evidence of systemic corticosteroid effects. Particular care should be taken in observing patients postoperatively or during periods of stress for evidence of inadequate adrenal response.

It is possible that systemic corticosteroid effects such as hypercorticism and adrenal suppression (including adrenal crisis) may appear in a small number of patients, particularly when FLOVENT HFA is administered at higher than recommended doses over prolonged periods of time. If such effects occur, the dosage of FLOVENT HFA should be reduced slowly, consistent with accepted procedures for reducing systemic corticosteroids and for management of asthma.

5.6 Hypersensitivity Reactions, Including Anaphylaxis

Hypersensitivity reactions, including anaphylaxis, angioedema, urticaria, and bronchospasm, may occur after administration of FLOVENT HFA [see Contraindications (4)].

5.7 Reduction in Bone Mineral Density

Decreases in bone mineral density (BMD) have been observed with long-term administration of products containing inhaled corticosteroids. The clinical significance of small changes in BMD with regard to long-term outcomes is unknown. Patients with major risk factors for decreased bone mineral content, such as prolonged immobilization, family history of osteoporosis, postmenopausal status, tobacco use, advanced age, poor nutrition, or chronic use of drugs that can reduce bone mass (e.g., anticonvulsants, oral corticosteroids), should be monitored and treated with established standards of care.

5.8 Effect on Growth

Orally inhaled corticosteroids may cause a reduction in growth velocity when administered to pediatric patients [see Use in Specific Populations (8.4)]. Monitor the growth of pediatric patients receiving FLOVENT HFA routinely (e.g., via stadiometry). To minimize the systemic effects of orally inhaled corticosteroids, including FLOVENT HFA, titrate each patient’s dosage to the lowest dosage that effectively controls his/her symptoms [see Dosage and Administration (2)].

5.9 Glaucoma and Cataracts

Glaucoma, increased intraocular pressure, and cataracts have been reported in patients following the long-term administration of inhaled corticosteroids, including fluticasone propionate. Therefore, close monitoring is warranted in patients with a change in vision or with a history of increased intraocular pressure, glaucoma, and/or cataracts.

5.10 Paradoxical Bronchospasm

As with other inhaled medications, bronchospasm may occur with an immediate increase in wheezing after dosing. If bronchospasm occurs following dosing with FLOVENT HFA, it should be treated immediately with a fast-acting inhaled bronchodilator. Treatment with FLOVENT HFA should be discontinued immediately and alternative therapy instituted.

5.11 Drug Interactions With Strong Cytochrome P450 3A4 Inhibitors

The use of strong cytochrome P450 3A4 (CYP3A4) inhibitors (e.g., ritonavir, atazanavir, clarithromycin, indinavir, itraconazole, nefazodone, nelfinavir, saquinavir, ketoconazole, telithromycin) with FLOVENT HFA is not recommended because increased systemic corticosteroid adverse effects may occur [see Drug Interactions (7.1), Clinical Pharmacology (12.3)].

5.12 Eosinophilic Conditions and Churg-Strauss Syndrome

In rare cases, patients on inhaled fluticasone propionate may present with systemic eosinophilic conditions. Some of these patients have clinical features of vasculitis consistent with Churg-Strauss syndrome, a condition that is often treated with systemic corticosteroid therapy. These events usually, but not always, have been associated with the reduction and/or withdrawal of oral corticosteroid therapy following the introduction of fluticasone propionate. Cases of serious eosinophilic conditions have also been reported with other inhaled corticosteroids in this clinical setting. Physicians should be alert to eosinophilia, vasculitic rash, worsening pulmonary symptoms, cardiac complications, and/or neuropathy presenting in their patients. A causal relationship between fluticasone propionate and these underlying conditions has not been established.

6 ADVERSE REACTIONS

Systemic and local corticosteroid use may result in the following:

- Candida albicans infection [see Warnings and Precautions (5.1)]
- Immunosuppression [see Warnings and Precautions (5.3)]
- Hypercorticism and adrenal suppression [see Warnings and Precautions (5.5)]
- Reduction in bone mineral density [see Warnings and Precautions (5.7)]
- Growth effects [see Warnings and Precautions (5.8)]
- Glaucoma and cataracts [see Warnings and Precautions (5.9)]

6.1 Clinical Trials Experience

Because clinical trials are conducted under widely varying conditions, adverse reaction rates observed in the clinical trials of a drug cannot be directly compared with rates in the clinical trials of another drug and may not reflect the rates observed in practice.

The incidence of common adverse reactions in Table 2 is based upon 2 placebo-controlled US clinical trials in which 812 adult and adolescent patients (457 females and 355 males) previously treated with as-needed bronchodilators and/or inhaled corticosteroids were treated twice daily for up to 12 weeks with 2 inhalations of FLOVENT HFA 44 mcg Inhalation Aerosol, FLOVENT HFA 110 mcg Inhalation Aerosol, FLOVENT HFA 220 mcg Inhalation Aerosol (dosages of 88, 220, or 440 mcg twice daily), or placebo.

Table 2. Adverse Reactions With >3% Incidence in US Controlled Clinical Trials With FLOVENT HFA in Patients Aged 12 Years and Older With Asthma Previously Receiving Bronchodilators and/or Inhaled Corticosteroids
Adverse Event | FLOVENT HFA; 88 mcg; Twice Daily; (n = 203); % | FLOVENT HFA; 220 mcg; Twice Daily; (n = 204); % | FLOVENT HFA; 440 mcg; Twice Daily; (n = 202); % | Placebo; (n = 203); %
Ear, nose, and throat
Upper respiratory tract infection | 18 | 16 | 16 | 14
Throat irritation | 8 | 8 | 10 | 5
Upper respiratory inflammation | 2 | 5 | 5 | 1
Sinusitis/sinus infection | 6 | 7 | 4 | 3
Hoarseness/dysphonia | 2 | 3 | 6 | <1
Gastrointestinal
Candidiasis mouth/throat & non-site specific | 4 | 2 | 5 | <1
Lower respiratory
Cough | 4 | 6 | 4 | 5
Bronchitis | 2 | 2 | 6 | 5
Neurological
Headache | 11 | 7 | 5 | 6

Table 2 includes all events (whether considered drug-related or nondrug-related by the investigator) that occurred at a rate of over 3% in any of the groups treated with FLOVENT HFA and were more common than in the placebo group. Less than 2% of patients discontinued from the studies because of adverse reactions. The average duration of exposure was 73 to 76 days in the active treatment groups compared with 60 days in the placebo group.

Additional Adverse Reactions: Other adverse reactions not previously listed, whether considered drug-related or not by the investigators, that were reported more frequently by patients with asthma treated with FLOVENT HFA compared with patients treated with placebo include the following: rhinitis, rhinorrhea/post-nasal drip, nasal sinus disorders, laryngitis, diarrhea, viral gastrointestinal infections, dyspeptic symptoms, gastrointestinal discomfort and pain, hyposalivation, musculoskeletal pain, muscle pain, muscle stiffness/tightness/rigidity, dizziness, migraines, fever, viral infections, pain, chest symptoms, viral skin infections, muscle injuries, soft tissue injuries, urinary infections.

Fluticasone propionate inhalation aerosol (440 or 880 mcg twice daily) was administered for 16 weeks to 168 patients with asthma requiring oral corticosteroids (Study 3). Adverse reactions not included above, but reported by more than 3 patients in either group treated with FLOVENT HFA and more commonly than in the placebo group included nausea and vomiting, arthralgia and articular rheumatism, and malaise and fatigue.

In 2 long-term studies (26 and 52 weeks), the pattern of adverse reactions in patients treated with FLOVENT HFA at dosages up to 440 mcg twice daily was similar to that observed in the 12-week studies. There were no new and/or unexpected adverse reactions with long-term treatment.

Pediatric Patients Aged 4 to 11 Years: FLOVENT HFA has been evaluated for safety in 56 pediatric patients who received 88 mcg twice daily for 4 weeks. Types of adverse reactions in these pediatric patients were generally similar to those observed in adults and adolescents.

6.2 Postmarketing Experience

In addition to adverse reactions reported from clinical trials, the following adverse reactions have been identified during postmarketing use of fluticasone propionate. Because these reactions are reported voluntarily from a population of uncertain size, it is not always possible to reliably estimate their frequency or establish a causal relationship to drug exposure. These events have been chosen for inclusion due to either their seriousness, frequency of reporting, or causal connection to fluticasone propionate or a combination of these factors.

Ear, Nose, and Throat: Aphonia, facial and oropharyngeal edema, and throat soreness and irritation.

Endocrine and Metabolic: Cushingoid features, growth velocity reduction in children/adolescents, hyperglycemia, osteoporosis, and weight gain.

Eye: Cataracts.

Gastrointestinal Disorders: Dental caries and tooth discoloration.

Psychiatry: Agitation, aggression, anxiety, depression, and restlessness. Behavioral changes, including hyperactivity and irritability, have been reported very rarely and primarily in children.

Immune System Disorders: Immediate and delayed hypersensitivity reactions, including urticaria, anaphylaxis, rash, and angioedema and bronchospasm, have been reported.

Respiratory: Asthma exacerbation, chest tightness, cough, dyspnea, immediate and delayed bronchospasm, paradoxical bronchospasm, pneumonia, and wheeze.

Skin: Contusions, cutaneous hypersensitivity reactions, ecchymoses, and pruritus.

Eosinophilic Conditions: In rare cases, patients on inhaled fluticasone propionate may present with systemic eosinophilic conditions, with some patients presenting with clinical features of vasculitis consistent with Churg-Strauss syndrome, a condition that is often treated with systemic corticosteroid therapy. These events usually, but not always, have been associated with the reduction and/or withdrawal of oral corticosteroid therapy following the introduction of fluticasone propionate [see Warnings and Precautions (5.12)].

7 DRUG INTERACTIONS

7.1 Strong Cytochrome P450 3A4 Inhibitors

Fluticasone propionate is a substrate of CYP3A4. The use of strong CYP3A4 inhibitors (e.g., ritonavir, atazanavir, clarithromycin, indinavir, itraconazole, nefazodone, nelfinavir, saquinavir, ketoconazole, telithromycin) with FLOVENT HFA is not recommended because increased systemic corticosteroid adverse effects may occur.

A drug interaction study with fluticasone propionate aqueous nasal spray in healthy subjects has shown that ritonavir (a strong CYP3A4 inhibitor) can significantly increase plasma fluticasone propionate concentration, resulting in significantly reduced serum cortisol concentrations [see Clinical Pharmacology (12.3)]. During postmarketing use, there have been reports of clinically significant drug interactions in patients receiving fluticasone propionate and ritonavir, resulting in systemic corticosteroid effects including Cushing’s syndrome and adrenal suppression. Therefore, coadministration of fluticasone propionate and ritonavir is not recommended unless the potential benefit to the patient outweighs the risk of systemic corticosteroid side effects.

Coadministration of orally inhaled fluticasone propionate (1,000 mcg) and ketoconazole (200 mg once daily) resulted in a 1.9-fold increase in plasma fluticasone propionate exposure and a 45% decrease in plasma cortisol area under the curve (AUC), but had no effect on urinary excretion of cortisol. Coadministration of fluticasone propionate and ketoconazole is not recommended unless the potential benefit to the patient outweighs the risk of systemic corticosteroid side effects.

8 USE IN SPECIFIC POPULATIONS

8.1 Pregnancy

Pregnancy Category C. There are no adequate and well-controlled studies with FLOVENT HFA in pregnant women. FLOVENT HFA should be used during pregnancy only if the potential benefit justifies the potential risk to the fetus.

Teratogenic Effects: Subcutaneous studies in mice at a dose approximately 0.1 times the maximum recommended human daily inhalation dose (MRHD) in adults on a mg/m^2 basis and in the rat at a dose approximately 0.5 times the MRHD in adults on a mg/m^2 basis revealed fetal toxicity characteristic of potent corticosteroid compounds, including embryonic growth retardation, omphalocele, cleft palate, and retarded cranial ossification.

In rabbits, fetal weight reduction and cleft palate were observed at a subcutaneous dose approximately 0.04 times the MRHD in adults on a mg/m^2 basis. However, no teratogenic effects were reported at oral doses up to approximately 3 times the MRHD in adults on a mg/m^2 basis. No fluticasone propionate was detected in the plasma in this study, consistent with the established low bioavailability following oral administration [see Clinical Pharmacology (12.3)].

Experience with oral corticosteroids since their introduction in pharmacologic, as opposed to physiologic, doses suggests that rodents are more prone to teratogenic effects from corticosteroids than humans. In addition, because there is a natural increase in corticosteroid production during pregnancy, most women will require a lower exogenous corticosteroid dose and many will not need corticosteroid treatment during pregnancy.

8.3 Nursing Mothers

It is not known whether fluticasone propionate is excreted in human breast milk. However, other corticosteroids have been detected in human milk. Subcutaneous administration to lactating rats of tritiated fluticasone propionate (approximately 0.05 times the MRHD in adults on a mg/m^2 basis) resulted in measurable radioactivity in milk.

Since there are no data from controlled trials on the use of FLOVENT HFA by nursing mothers, caution should be exercised when FLOVENT HFA is administered to a nursing woman.

8.4 Pediatric Use

The safety and effectiveness of FLOVENT HFA in children 4 years and older have been established [see Adverse Reactions (6.1), Clinical Pharmacology (12.3), Clinical Studies (14.2)]. The safety and effectiveness of FLOVENT HFA in children younger than 4 years have not been established. Use of FLOVENT HFA in patients aged 4 to 11 years is supported by evidence from adequate and well-controlled studies in adults and adolescents 12 years and older, pharmacokinetic studies in patients aged 4 to 11 years, established efficacy of fluticasone propionate formulated as FLOVENT® DISKUS® (fluticasone propionate inhalation powder) and FLOVENT® ROTADISK® (fluticasone propionate inhalation powder) in patients aged 4 to 11 years, and supportive findings with FLOVENT HFA in a study conducted in patients aged 4 to 11 years.

Effects on Growth: Orally inhaled corticosteroids may cause a reduction in growth velocity when administered to pediatric patients. A reduction of growth velocity in children or teenagers may occur as a result of poorly controlled asthma or from use of corticosteroids including inhaled corticosteroids. The effects of long-term treatment of children and adolescents with inhaled corticosteroids, including fluticasone propionate, on final adult height are not known.

Controlled clinical studies have shown that inhaled corticosteroids may cause a reduction in growth in pediatric patients. In these studies, the mean reduction in growth velocity was approximately 1 cm/year (range: 0.3 to 1.8 cm/year) and appears to depend upon dose and duration of exposure. This effect was observed in the absence of laboratory evidence of HPA axis suppression, suggesting that growth velocity is a more sensitive indicator of systemic corticosteroid exposure in pediatric patients than some commonly used tests of HPA axis function. The long-term effects of this reduction in growth velocity associated with orally inhaled corticosteroids, including the impact on final adult height, are unknown. The potential for “catch-up” growth following discontinuation of treatment with orally inhaled corticosteroids has not been adequately studied. The effects on growth velocity of treatment with orally inhaled corticosteroids for over 1 year, including the impact on final adult height, are unknown. The growth of children and adolescents receiving orally inhaled corticosteroids, including FLOVENT HFA, should be monitored routinely (e.g., via stadiometry). The potential growth effects of prolonged treatment should be weighed against the clinical benefits obtained and the risks associated with alternative therapies. To minimize the systemic effects of orally inhaled corticosteroids, including FLOVENT HFA, each patient should be titrated to the lowest dose that effectively controls his/her symptoms.

Since a cross study comparison in adolescent and adult patients (aged 12 years and older) indicated that systemic exposure of inhaled fluticasone propionate from FLOVENT HFA would be higher than exposure from FLOVENT ROTADISK, results from a study to assess the potential growth effects of FLOVENT ROTADISK in pediatric patients (aged 4 to 11 years) are provided.

A 52-week placebo-controlled study to assess the potential growth effects of fluticasone propionate inhalation powder (FLOVENT ROTADISK) at 50 and 100 mcg twice daily was conducted in the US in 325 prepubescent children (244 males and 81 females) aged 4 to 11 years. The mean growth velocities at 52 weeks observed in the intent-to-treat population were 6.32 cm/year in the placebo group (n = 76), 6.07 cm/year in the 50-mcg group (n = 98), and 5.66 cm/year in the 100-mcg group (n = 89). An imbalance in the proportion of children entering puberty between groups and a higher dropout rate in the placebo group due to poorly controlled asthma may be confounding factors in interpreting these data. A separate subset analysis of children who remained prepubertal during the study revealed growth rates at 52 weeks of 6.10 cm/year in the placebo group (n = 57), 5.91 cm/year in the 50-mcg group (n = 74), and 5.67 cm/year in the 100-mcg group (n = 79). In children aged 8.5 years, the mean age of children in this study, the range for expected growth velocity is: boys – 3rd percentile = 3.8 cm/year, 50th percentile = 5.4 cm/year, and 97th percentile = 7.0 cm/year; girls – 3rd percentile = 4.2 cm/year, 50th percentile = 5.7 cm/year, and 97th percentile = 7.3 cm/year.

The clinical significance of these growth data is not certain. Physicians should closely follow the growth of children and adolescents taking corticosteroids by any route, and weigh the benefits of corticosteroid therapy against the possibility of growth suppression if growth appears slowed. Patients should be maintained on the lowest dose of inhaled corticosteroid that effectively controls their asthma.

Children Younger Than 4 Years: Pharmacokinetics:[see Clinical Pharmacology (12.3)].

Pharmacodynamics: A 12-week, double-blind, placebo-controlled, parallel-group study was conducted in children with asthma aged 1 to less than 4 years. Twelve-hour overnight urinary cortisol excretion after a 12-week treatment period with 88 mcg of FLOVENT HFA twice daily (n = 73) and with placebo (n = 42) were calculated. The mean and median change from baseline in urine cortisol over 12 hours were -0.7 and 0.0 mcg for FLOVENT HFA and 0.3 and -0.2 mcg for placebo, respectively.

In a 1-way crossover study in children aged 6 to less than 12 months with reactive airways disease (N = 21), serum cortisol was measured over a 12-hour dosing period. Patients received placebo treatment for a 2-week period followed by a 4-week treatment period with 88 mcg of FLOVENT HFA twice daily with an AeroChamber Plus® Valved Holding Chamber (VHC) with face mask. The geometric mean ratio of serum cortisol over 12 hours (AUC0-12 hr) following FLOVENT HFA (n = 16) versus placebo (n = 18) was 0.95 (95% CI: 0.72, 1.27).

Safety: FLOVENT HFA administered as 88 mcg twice daily has been evaluated for safety in 239 pediatric patients aged 1 to less than 4 years in a 12-week, double-blind, placebo-controlled study. Treatments were administered with an AeroChamber Plus VHC with face mask. In pediatric patients aged 1 to less than 4 years receiving FLOVENT HFA, the following events occurred with a frequency greater than 3% and more frequently than in pediatric patients who received placebo, regardless of causality assessment: pyrexia, nasopharyngitis, upper respiratory tract infection, vomiting, otitis media, diarrhea, bronchitis, pharyngitis, and viral infection.

FLOVENT HFA administered as 88 mcg twice daily has also been evaluated for safety in 23 pediatric patients aged 6 to 12 months in an open-label placebo-controlled study. Treatments were administered with an AeroChamber Plus VHC with face mask for 2 weeks with placebo followed by 4 weeks with active drug. There was no discernable difference in the types of adverse events reported between patients receiving placebo compared to the active drug.

In Vitro Testing of Dose Delivery With Holding Chambers: In vitro dose characterization studies were performed to evaluate the delivery of FLOVENT HFA via holding chambers with attached face masks. The studies were conducted with 2 different holding chambers (AeroChamber Plus VHC and AeroChamber Z-STAT Plus™ VHC) and face masks (small and medium size) at inspiratory flow rates of 4.9, 8.0, and 12.0 L/min in combination with holding times of 0, 2, 5, and 10 seconds. The flow rates were selected to be representative of inspiratory flow rates of children aged 6 to 12 months, 2 to 5 years, and over 5 years, respectively. The mean delivered dose of fluticasone propionate through the holding chambers with face masks was lower than the 44 mcg of fluticasone propionate delivered directly from the actuator mouthpiece. The results were similar through both holding chambers (see Table 3 for data for the AeroChamber Plus VHC). The fine particle fraction (approximately 1 to 5 μm) across the flow rates used in these studies was 70% to 84% of the delivered dose, consistent with the removal of the coarser fraction by the holding chamber. In contrast, the fine particle fraction for FLOVENT HFA delivered without a holding chamber typically represents 42% to 55% of the delivered dose measured at the standard flow rate of 28.3 L/min. These data suggest that, on a per kilogram basis, young children receive a comparable dose of fluticasone propionate when delivered via a holding chamber and face mask as adults do without their use.

Table 3. In Vitro Medication Delivery Through AeroChamber Plus Valved Holding Chamber With a Face Mask
Age | Face Mask | Flow Rate; (L/min) | Holding Time; (seconds) | Mean Medication Delivery Through AeroChamber Plus VHC; (mcg/actuation) | Body Weight 50th Percentile; (kg)a | Medication Delivered per Actuation; (mcg/kg)b
6 to 12; Months | Small | 4.9 | 0; 2; 5; 10 | 8.3; 6.7; 7.5; 7.5 | 7.5-9.9 | 0.8-1.1; 0.7-0.9; 0.8-1.0; 0.8-1.0
2 to 5; Years | Small | 8.0 | 0; 2; 5; 10 | 7.3; 6.8; 6.7; 7.7 | 12.3-18.0 | 0.4-0.6; 0.4-0.6; 0.4-0.5; 0.4-0.6
2 to 5; Years | Medium | 8.0 | 0; 2; 5; 10 | 7.8; 7.7; 8.1; 9.0 | 12.3-18.0 | 0.4-0.6; 0.4-0.6; 0.5-0.7; 0.5-0.7
>5 Years | Medium | 12.0 | 0; 2; 5; 10 | 12.3; 11.8; 12.0; 10.1 | 18.0 | 0.7; 0.7; 0.7; 0.6

a Centers for Disease Control growth charts, developed by the National Center for Health Statistics in collaboration with the National Center for Chronic Disease Prevention and Health Promotion (2000). Ranges correspond to the average of the 50th percentile weight for boys and girls at the ages indicated.

b A single inhalation of FLOVENT HFA in a 70-kg adult without use of a valved holding chamber and face mask delivers approximately 44 mcg, or 0.6 mcg/kg.

8.5 Geriatric Use

Of the total number of patients treated with FLOVENT HFA in US and non-US clinical trials, 173 were 65 years or older, 19 of which were 75 years or older. No overall differences in safety or effectiveness were observed between these patients and younger patients, and other reported clinical experience has not identified differences in responses between the elderly and younger patients, but greater sensitivity of some older individuals cannot be ruled out.

8.6 Hepatic Impairment

Formal pharmacokinetic studies using FLOVENT HFA have not been conducted in patients with hepatic impairment. Since fluticasone propionate is predominantly cleared by hepatic metabolism, impairment of liver function may lead to accumulation of fluticasone propionate in plasma. Therefore, patients with hepatic disease should be closely monitored.

8.7 Renal Impairment

Formal pharmacokinetic studies using FLOVENT HFA have not been conducted in patients with renal impairment.

10 OVERDOSAGE

Chronic overdosage may result in signs/symptoms of hypercorticism [see Warnings and Precautions (5.5)]. Inhalation by healthy volunteers of a single dose of 1,760 or 3,520 mcg of fluticasone propionate CFC inhalation aerosol was well tolerated. Doses of 1,320 mcg administered to healthy human volunteers twice daily for 7 to 15 days were also well tolerated. Repeat oral doses up to 80 mg daily for 10 days in healthy volunteers and repeat oral doses up to 20 mg daily for 42 days in patients were well tolerated. Adverse reactions were of mild or moderate severity, and incidences were similar in active and placebo treatment groups.

No deaths were seen in mice given an oral dose of 1,000 mg/kg (approximately 2,300 and 11,000 times the MRHD for adults and children aged 4 to 11 years, respectively, on a mg/m^2 basis). No deaths were seen in rats given an oral dose of 1,000 mg/kg (approximately 4,600 and 22,000 times the MRHD in adults and children aged 4 to 11 years, respectively, on a mg/m^2 basis).

11 DESCRIPTION

The active component of FLOVENT HFA 44 mcg Inhalation Aerosol, FLOVENT HFA 110 mcg Inhalation Aerosol, and FLOVENT HFA 220 mcg Inhalation Aerosol is fluticasone propionate, a corticosteroid having the chemical name S-(fluoromethyl) 6α,9-difluoro-11β,17-dihydroxy-16α-methyl-3-oxoandrosta-1,4-diene-17β-carbothioate, 17-propionate and the following chemical structure:

Fluticasone propionate is a white powder with a molecular weight of 500.6, and the empirical formula is C25H31F3O5S. It is practically insoluble in water, freely soluble in dimethyl sulfoxide and dimethylformamide, and slightly soluble in methanol and 95% ethanol.

FLOVENT HFA 44 mcg Inhalation Aerosol, FLOVENT HFA 110 mcg Inhalation Aerosol, and FLOVENT HFA 220 mcg Inhalation Aerosol are pressurized metered-dose aerosol units fitted with a counter. FLOVENT HFA is intended for oral inhalation only. Each unit contains a microcrystalline suspension of fluticasone propionate (micronized) in propellant HFA-134a (1,1,1,2-tetrafluoroethane). It contains no other excipients.

After priming, each actuation of the inhaler delivers 50, 125, or 250 mcg of fluticasone propionate in 60 mg of suspension (for the 44-mcg product) or in 75 mg of suspension (for the 110- and 220-mcg products) from the valve. Each actuation delivers 44, 110, or 220 mcg of fluticasone propionate from the actuator. The actual amount of drug delivered to the lung may depend on patient factors, such as the coordination between the actuation of the device and inspiration through the delivery system.

Each 10.6-g canister (44 mcg) and each 12-g canister (110 and 220 mcg) provides 120 inhalations.

FLOVENT HFA should be primed before using for the first time by releasing 4 test sprays into the air away from the face, shaking well for 5 seconds before each spray. In cases where the inhaler has not been used for more than 7 days or when it has been dropped, prime the inhaler again by shaking well for 5 seconds and releasing 1 test spray into the air away from the face.

This product does not contain any chlorofluorocarbon (CFC) as the propellant.

12 CLINICAL PHARMACOLOGY

12.1 Mechanism of Action

Fluticasone propionate is a synthetic trifluorinated corticosteroid with potent anti-inflammatory activity. In vitro assays using human lung cytosol preparations have established fluticasone propionate as a human glucocorticoid receptor agonist with an affinity 18 times greater than dexamethasone, almost twice that of beclomethasone17monopropionate (BMP), the active metabolite of beclomethasone dipropionate, and over 3 times that of budesonide. Data from the McKenzie vasoconstrictor assay in man are consistent with these results. The clinical significance of these findings is unknown.

Inflammation is an important component in the pathogenesis of asthma. Corticosteroids have been shown to inhibit multiple cell types (e.g., mast cells, eosinophils, basophils, lymphocytes, macrophages, neutrophils) and mediator production or secretion (e.g., histamine, eicosanoids, leukotrienes, cytokines) involved in the asthmatic response. These anti-inflammatory actions of corticosteroids contribute to their efficacy in asthma.

Though effective for the treatment of asthma, corticosteroids do not affect asthma symptoms immediately. Individual patients will experience a variable time to onset and degree of symptom relief. Maximum benefit may not be achieved for 1 to 2 weeks or longer after starting treatment. When corticosteroids are discontinued, asthma stability may persist for several days or longer.

Studies in patients with asthma have shown a favorable ratio between topical anti-inflammatory activity and systemic corticosteroid effects with recommended doses of orally inhaled fluticasone propionate. This is explained by a combination of a relatively high local anti-inflammatory effect, negligible oral systemic bioavailability (less than 1%), and the minimal pharmacological activity of the only metabolite detected in man.

12.2 Pharmacodynamics

Serum cortisol concentrations, urinary excretion of cortisol, and urine 6-β-hydroxycortisol excretion collected over 24 hours in 24 healthy subjects following 8 inhalations of fluticasone propionate HFA 44, 110, and 220 mcg decreased with increasing dose. However, in patients with asthma treated with 2 inhalations of fluticasone propionate HFA 44, 110, and 220 mcg twice daily for at least 4 weeks, differences in serum cortisol AUC(0-12 hr) (n = 65) and 24-hour urinary excretion of cortisol (n = 47) compared with placebo were not related to dose and generally not significant. In the study with healthy volunteers, the effect of propellant was also evaluated by comparing results following the 220-mcg strength inhaler containing HFA 134a propellant with the same strength of inhaler containing CFC 11/12 propellant. A lesser effect on the HPA axis with the HFA formulation was observed for serum cortisol, but not urine cortisol and 6-betahydroxy cortisol excretion. In addition, in a crossover study of children with asthma aged 4 to 11 years (N = 40), 24-hour urinary excretion of cortisol was not affected after a 4-week treatment period with 88 mcg of fluticasone propionate HFA twice daily compared with urinary excretion after the 2-week placebo period. The ratio (95% CI) of urinary excretion of cortisol over 24 hours following fluticasone propionate HFA versus placebo was 0.987 (0.796, 1.223).

The potential systemic effects of fluticasone propionate HFA on the HPA axis were also studied in patients with asthma. Fluticasone propionate given by inhalation aerosol at dosages of 440 or 880 mcg twice daily was compared with placebo in oral corticosteroid-dependent patients with asthma (range of mean dose of prednisone at baseline: 13 to 14 mg/day) in a 16-week study. Consistent with maintenance treatment with oral corticosteroids, abnormal plasma cortisol responses to short cosyntropin stimulation (peak plasma cortisol less than 18 mcg/dL) were present at baseline in the majority of patients participating in this study (69% of patients later randomized to placebo and 72% to 78% of patients later randomized to fluticasone propionate HFA). At week 16, 8 patients (73%) on placebo compared with 14 (54%) and 13 (68%) patients receiving fluticasone propionate HFA (440 and 880 mcg twice daily, respectively) had post-stimulation cortisol levels of less than 18 mcg/dL.

12.3 Pharmacokinetics

Absorption: Fluticasone propionate acts locally in the lung; therefore, plasma levels do not predict therapeutic effect. Studies using oral dosing of labeled and unlabeled drug have demonstrated that the oral systemic bioavailability of fluticasone propionate is negligible (less than 1%), primarily due to incomplete absorption and presystemic metabolism in the gut and liver. In contrast, the majority of the fluticasone propionate delivered to the lung is systemically absorbed.

Distribution: Following intravenous administration, the initial disposition phase for fluticasone propionate was rapid and consistent with its high lipid solubility and tissue binding. The volume of distribution averaged 4.2 L/kg.

The percentage of fluticasone propionate bound to human plasma proteins averages 99%. Fluticasone propionate is weakly and reversibly bound to erythrocytes and is not significantly bound to human transcortin.

Metabolism: The total clearance of fluticasone propionate is high (average, 1,093 mL/min), with renal clearance accounting for less than 0.02% of the total. The only circulating metabolite detected in man is the 17β-carboxylic acid derivative of fluticasone propionate, which is formed through the CYP 3A4 pathway. This metabolite had less affinity (approximately 1/2,000) than the parent drug for the corticosteroid receptor of human lung cytosol in vitro and negligible pharmacological activity in animal studies. Other metabolites detected in vitro using cultured human hepatoma cells have not been detected in man.

Elimination: Following intravenous dosing, fluticasone propionate showed polyexponential kinetics and had a terminal elimination half-life of approximately 7.8 hours. Less than 5% of a radiolabeled oral dose was excreted in the urine as metabolites, with the remainder excreted in the feces as parent drug and metabolites.

Specific Populations: Gender: No significant difference in clearance (CL/F) of fluticasone propionate was observed.

Pediatrics: A population pharmacokinetic analysis was performed for FLOVENT HFA using steady-state data from 4 controlled clinical trials and single-dose data from 1 controlled clinical trial. The combined cohort for analysis included 269 patients (161 males and 108 females) with asthma aged 6 months to 66 years who received treatment with FLOVENT HFA. Most of these subjects (n = 215) were treated with FLOVENT HFA 44 mcg given as 88 mcg twice daily. FLOVENT HFA was delivered using an AeroChamber Plus VHC with a face mask to patients aged less than 4 years. Data from adult patients with asthma following FLOVENT HFA 110 mcg given as 220 mcg twice daily (n = 15) and following FLOVENT HFA 220 mcg given as 440 mcg twice daily (n = 17) at steady state were also included. Data for 22 patients came from a single-dose crossover study of 264 mcg (6 doses of FLOVENT HFA 44 mcg) with and without AeroChamber Plus VHC in children with asthma aged 4 to 11 years.

Stratification of exposure data following FLOVENT HFA 88 mcg by age and study indicated that systemic exposure to fluticasone propionate at steady state was similar in children aged 6 to less than 12 months, children aged 1 to less than 4 years, and adults and adolescents aged 12 years and older. Exposure was lower in children aged 4 to 11 years, who did not use a VHC, as shown in Table 4.

Table 4. Systemic Exposure to Fluticasone Propionate Following FLOVENT HFA 88 mcg Twice Daily
Age | Valved Holding Chamber | N | AUC0-τ, pg•hr/mL; (95% CI) | Cmax, pg/mL; (95% CI)
6 to <12 Months | Yes | 17 | 141 (88, 227) | 19 (13, 29)
1 to <4 Years | Yes | 164 | 143 (131, 157) | 20 (18, 21)
4 to 11 Years | No | 14 | 68 (48, 97) | 11 (8, 16)
≥12 Years | No | 20 | 149 (106, 210) | 20 (15, 27)

The lower exposure to fluticasone propionate in children aged 4 to 11 years who did not use a VHC may reflect the inability to coordinate actuation and inhalation of the metered-dose inhaler. The impact of the use of a VHC on exposure to fluticasone propionate in patients aged 4 to 11 years was evaluated in a single-dose crossover study with FLOVENT HFA 44 mcg given as 264 mcg. In this study, use of a VHC increased systemic exposure to fluticasone propionate (Table 5), possibly correcting for the inability to coordinate actuation and inhalation.

Table 5. Systemic Exposure to Fluticasone Propionate Following a Single Dose of FLOVENT HFA 264 mcg
Age | Valved Holding Chamber | N | AUC(0-∞), pg•hr/mL; (95% CI) | Cmax, pg/mL; (95% CI)
4 to 11 Years | Yes | 22 | 373 (297, 468) | 61 (51, 73)
4 to 11 Years | No | 21 | 141 (111, 178) | 23 (19, 28)

There was a dose-related increase in systemic exposure in patients aged 12 years and older receiving higher doses of fluticasone propionate (220 and 440 mcg twice daily). The AUC0-τ in pg•hr/mL was 358 (95% CI: 272, 473) and 640 (95% CI: 477, 858), and Cmax in pg/mL was 47.3 (95% CI: 37, 61) and 87 (95% CI: 68, 112) following fluticasone propionate 220 and 440 mcg, respectively.

Hepatic and Renal Impairment: Formal pharmacokinetic studies using FLOVENT HFA have not been conducted in patients with hepatic or renal impairment. However, since fluticasone propionate is predominantly cleared by hepatic metabolism, impairment of liver function may lead to accumulation of fluticasone propionate in plasma. Therefore, patients with hepatic disease should be closely monitored.

Race: No significant difference in clearance (CL/F) of fluticasone propionate in Caucasian, African-American, Asian, or Hispanic populations was observed.

Drug Interactions: Ritonavir: Fluticasone propionate is a substrate of CYP3A4. Coadministration of fluticasone propionate and the strong CYP3A4 inhibitor ritonavir is not recommended based upon a multiple-dose, crossover drug interaction study in 18 healthy subjects. Fluticasone propionate aqueous nasal spray (200 mcg once daily) was coadministered for 7 days with ritonavir (100 mg twice daily). Plasma fluticasone propionate concentrations following fluticasone propionate aqueous nasal spray alone were undetectable (less than 10 pg/mL) in most subjects, and when concentrations were detectable, peak levels (Cmax) averaged 11.9 pg/mL (range: 10.8 to 14.1 pg/mL) and AUC(0-τ) averaged 8.43 pg•hr/mL (range: 4.2 to 18.8 pg•hr/mL). Fluticasone propionate Cmax and AUC(0-τ) increased to 318 pg/mL (range: 110 to 648 pg/mL) and 3,102.6 pg•hr/mL (range: 1,207.1 to 5,662.0 pg•hr/mL), respectively, after coadministration of ritonavir with fluticasone propionate aqueous nasal spray. This significant increase in plasma fluticasone propionate exposure resulted in a significant decrease (86%) in serum cortisol AUC.

Ketoconazole: In a placebo-controlled, crossover study in 8 healthy adult volunteers, coadministration of a single dose of orally inhaled fluticasone propionate (1,000 mcg) with multiple doses of ketoconazole (200 mg) to steady state resulted in increased plasma fluticasone propionate exposure, a reduction in plasma cortisol AUC, and no effect on urinary excretion of cortisol.

Following orally inhaled fluticasone propionate alone, AUC(2-last) averaged 1.559 ng•hr/mL (range: 0.555 to 2.906 ng•hr/mL) and AUC(2-∞) averaged 2.269 ng•hr/mL (range: 0.836 to 3.707 ng•hr/mL). Fluticasone propionate AUC(2-last) and AUC(2-∞) increased to 2.781 ng•hr/mL (range: 2.489 to 8.486 ng•hr/mL) and 4.317 ng•hr/mL (range: 3.256 to 9.408 ng•hr/mL), respectively, after coadministration of ketoconazole with orally inhaled fluticasone propionate. This increase in plasma fluticasone propionate concentration resulted in a decrease (45%) in serum cortisol AUC.

Erythromycin: In a multiple-dose drug interaction study, coadministration of orally inhaled fluticasone propionate (500 mcg twice daily) and erythromycin (333 mg 3 times daily) did not affect fluticasone propionate pharmacokinetics.

13 NONCLINICAL TOXICOLOGY

13.1 Carcinogenesis, Mutagenesis, Impairment of Fertility

Fluticasone propionate demonstrated no tumorigenic potential in mice at oral doses up to 1,000 mcg/kg (approximately 2 and 10 times the MRHD in adults and children aged 4 to 11 years, respectively, on a mg/m^2 basis) for 78 weeks or in rats at inhalation doses up to 57 mcg/kg (approximately 0.3 times and approximately equivalent to the MRHD in adults and children aged 4 to 11 years, respectively, on a mg/m^2 basis) for 104 weeks.

Fluticasone propionate did not induce gene mutation in prokaryotic or eukaryotic cells in vitro. No significant clastogenic effect was seen in cultured human peripheral lymphocytes in vitro or in the in vivo mouse micronucleus test.

No evidence of impairment of fertility was observed in reproductive studies conducted in male and female rats at subcutaneous doses up to 50 mcg/kg (approximately 0.2 times the MRHD in adults on a mg/m^2 basis). Prostate weight was significantly reduced at a subcutaneous dose of 50 mcg/kg.

13.2 Animal Toxicology and/or Pharmacology

Reproductive Toxicology: Subcutaneous studies in mice and rats at 45 and 100 mcg/kg (approximately 0.1 and 0.5 times the MRHD in adults on a mg/m^2 basis, respectively) revealed fetal toxicity characteristic of potent corticosteroid compounds, including embryonic growth retardation, omphalocele, cleft palate, and retarded cranial ossification.

In rabbits, fetal weight reduction and cleft palate were observed at a subcutaneous dose of 4 mcg/kg (approximately 0.04 times the MRHD in adults on a mg/m^2 basis). However, no teratogenic effects were reported at oral doses up to 300 mcg/kg (approximately 3 times the MRHD in adults on a mg/m^2 basis) of fluticasone propionate. No fluticasone propionate was detected in the plasma in this study, consistent with the established low bioavailability following oral administration [see Clinical Pharmacology (12.3)].

Fluticasone propionate crossed the placenta following subcutaneous administration to mice and rats and oral administration to rabbits.

In animals and humans, propellant HFA-134a was found to be rapidly absorbed and rapidly eliminated, with an elimination half-life of 3 to 27 minutes in animals and 5 to 7 minutes in humans. Time to maximum plasma concentration (Tmax) and mean residence time are both extremely short, leading to a transient appearance of HFA-134a in the blood with no evidence of accumulation.

Propellant HFA-134a is devoid of pharmacological activity except at very high doses in animals (i.e., 380 to 1,300 times the maximum human exposure based on comparisons of AUC values), primarily producing ataxia, tremors, dyspnea, or salivation. These events are similar to effects produced by the structurally related CFCs, which have been used extensively in metered-dose inhalers.

14 CLINICAL STUDIES

14.1 Adult and Adolescent Patients Aged 12 Years and Older

Three randomized, double-blind, parallel-group, placebo-controlled, US clinical trials were conducted in 980 adult and adolescent patients (aged 12 years and older) with asthma to assess the efficacy and safety of FLOVENT HFA in the treatment of asthma. Fixed dosages of 88, 220, and 440 mcg twice daily (each dose administered as 2 inhalations of the 44-, 110-, and 220-mcg strengths, respectively) and 880 mcg twice daily (administered as 4 inhalations of the 220-mcg strength) were compared with placebo to provide information about appropriate dosing to cover a range of asthma severity. Patients in these studies included those inadequately controlled with bronchodilators alone (Study 1), those already receiving inhaled corticosteroids (Study 2), and those requiring oral corticosteroid therapy (Study 3). In all 3 studies, patients (including placebo-treated patients) were allowed to use VENTOLIN® (albuterol, USP) Inhalation Aerosol as needed for relief of acute asthma symptoms. In Studies 1 and 2, other maintenance asthma therapies were discontinued.

Study 1 enrolled 397 patients with asthma inadequately controlled on bronchodilators alone. FLOVENT HFA was evaluated at dosages of 88, 220, and 440 mcg twice daily for 12 weeks. Baseline FEV1 values were similar across groups (mean 67% of predicted normal). All 3 dosages of FLOVENT HFA demonstrated a statistically significant improvement in lung function as measured by improvement in AM pre-dose FEV1 compared with placebo. This improvement was observed after the first week of treatment, and was maintained over the 12-week treatment period.

At Endpoint (last observation), mean change from baseline in AM pre-dose percent predicted FEV1 was greater in all 3 groups treated with FLOVENT HFA (9.0% to 11.2%) compared with the placebo group (3.4%). The mean differences between the groups treated with FLOVENT HFA 88, 220, and 440 mcg and the placebo group were statistically significant, and the corresponding 95% confidence intervals were (2.2%, 9.2%), (2.8%, 9.9%), and (4.3%, 11.3%), respectively.

Figure 1 displays results of pulmonary function tests (mean percent change from baseline in FEV1 prior to AM dose) for the recommended starting dosage of FLOVENT HFA (88 mcg twice daily) and placebo from Study 1. This trial used predetermined criteria for lack of efficacy (indicators of worsening asthma), resulting in withdrawal of more patients in the placebo group. Therefore, pulmonary function results at Endpoint (the last evaluable FEV1 result, including most patients’ lung function data) are also displayed.

Figure 1. A 12-Week Clinical Trial in Patients Aged 12 Years and Older Inadequately Controlled on Bronchodilators Alone: Mean Percent Change From Baseline in FEV1 Prior to AM Dose (Study 1)

In Study 2, FLOVENT HFA at dosages of 88, 220, and 440 mcg twice daily was evaluated over 12 weeks of treatment in 415 patients with asthma who were already receiving an inhaled corticosteroid at a daily dose within its recommended dose range in addition to as-needed albuterol. Baseline FEV1 values were similar across groups (mean 65% to 66% of predicted normal). All 3 dosages of FLOVENT HFA demonstrated a statistically significant improvement in lung function, as measured by improvement in FEV1, compared with placebo. This improvement was observed after the first week of treatment and was maintained over the 12-week treatment period. Discontinuations from the study for lack of efficacy (defined by a pre-specified decrease in FEV1 or PEF, or an increase in use of VENTOLIN or nighttime awakenings requiring treatment with VENTOLIN) were lower in the groups treated with FLOVENT HFA (6% to 11%) compared with placebo (50%).

At Endpoint (last observation), mean change from baseline in AM pre-dose percent predicted FEV1 was greater in all 3 groups treated with FLOVENT HFA (2.2% to 4.6%) compared with the placebo group (-8.3%). The mean differences between the groups treated with FLOVENT HFA 88, 220, and 440 mcg and the placebo group were statistically significant, and the corresponding 95% confidence intervals were (7.1%, 13.8%), (8.2%, 14.9%), and (9.6%, 16.4%), respectively.

Figure 2 displays the mean percent change from baseline in FEV1 from Week 1 through Week 12. This study also used predetermined criteria for lack of efficacy, resulting in withdrawal of more patients in the placebo group; therefore, pulmonary function results at Endpoint are also displayed.

Figure 2. A 12-Week Clinical Trial in Patients Aged 12 Years and Older Already Receiving Daily Inhaled Corticosteroids: Mean Percent Change From Baseline in FEV1 Prior to AM Dose (Study 2)

In both studies, use of VENTOLIN, AM and PM PEF, and asthma symptom scores showed numerical improvement with FLOVENT HFA compared with placebo.

Study 3 enrolled 168 patients with asthma requiring oral prednisone therapy (average baseline daily prednisone dose ranged from 13 to 14 mg). FLOVENT HFA at dosages of 440 and 880 mcg twice daily was evaluated over a 16-week treatment period. Baseline FEV1 values were similar across groups (mean 59% to 62% of predicted normal). Over the course of the study, patients treated with either dosage of FLOVENT HFA required a statistically significantly lower mean daily oral prednisone dose (6 mg) compared with placebo-treated patients (15 mg). Both dosages of FLOVENT HFA enabled a larger percentage of patients (59% and 56% in the groups treated with FLOVENT HFA 440 and 880 mcg, respectively, twice daily) to eliminate oral prednisone as compared with placebo (13%) (see Figure 3). There was no efficacy advantage of FLOVENT HFA 880 mcg twice daily compared with 440 mcg twice daily. Accompanying the reduction in oral corticosteroid use, patients treated with either dosage of FLOVENT HFA had statistically significantly improved lung function, fewer asthma symptoms, and less use of VENTOLIN Inhalation Aerosol compared with the placebo-treated patients.

Figure 3. A 16-Week Clinical Trial in Patients Aged 12 Years and Older Requiring Chronic Oral Prednisone Therapy: Change in Maintenance Prednisone Dose

Two long-term safety studies (Study 4 and Study 5) of ≥6 months’ duration were conducted in 507 adult and adolescent patients with asthma. Study 4 was designed to monitor the safety of 2 doses of FLOVENT HFA, while Study 5 compared fluticasone propionate HFA with fluticasone propionate CFC. Study 4 enrolled 182 patients who were treated daily with low to high doses of inhaled corticosteroids, beta-agonists (short-acting [as needed or regularly scheduled] or long-acting), theophylline, inhaled cromolyn or nedocromil sodium, leukotriene receptor antagonists, or 5-lipoxygenase inhibitors at baseline. FLOVENT HFA at dosages of 220 and 440 mcg twice daily was evaluated over a 26-week treatment period in 89 and 93 patients, respectively. Study 5 enrolled 325 patients who were treated daily with moderate to high doses of inhaled corticosteroids, with or without concurrent use of salmeterol or albuterol, at baseline. Fluticasone propionate HFA at a dosage of 440 mcg twice daily and fluticasone propionate CFC at a dosage of 440 mcg twice daily were evaluated over a 52-week treatment period in 163 and 162 patients, respectively. Baseline FEV1 values were similar across groups (mean 81% to 84% of predicted normal). Throughout the 52-week treatment period, asthma control was maintained with both formulations of fluticasone propionate compared with baseline. In both studies, none of the patients were withdrawn due to lack of efficacy.

14.2 Pediatric Patients Aged 4 to 11 Years

A 12-week clinical trial conducted in 241 pediatric patients with asthma was supportive of efficacy but inconclusive due to measurable levels of fluticasone propionate in 6/48 (13%) of the plasma samples from patients randomized to placebo. Efficacy in patients aged 4 to 11 years is extrapolated from adult data with FLOVENT HFA and other supporting data [see Use in Specific Populations (8.4)].

16 HOW SUPPLIED/STORAGE AND HANDLING

FLOVENT HFA 44 mcg Inhalation Aerosol is supplied in 10.6-g pressurized aluminum canisters containing 120 metered inhalations in boxes of 1 (NDC 54868-5995-0).

FLOVENT HFA 110 mcg Inhalation Aerosol is supplied in 12-g pressurized aluminum canisters containing 120 metered inhalations in boxes of 1 (NDC 54868-5362-0).

FLOVENT HFA 220 mcg Inhalation Aerosol is supplied in 12-g pressurized aluminum canisters containing 120 metered inhalations in boxes of 1 (NDC 54868-5637-0).

Each canister is fitted with a counter and a dark orange oral actuator with a peach strapcap packaged within a plastic-coated, moisture-protective foil pouch and patient’s instructions. The moisture-protective foil pouch also contains a desiccant that should be discarded when the pouch is opened.

The dark orange actuator supplied with FLOVENT HFA should not be used with any other product canisters, and actuators from other products should not be used with a FLOVENT HFA canister.

The correct amount of medication in each inhalation cannot be assured after the counter reads 000, even though the canister is not completely empty and will continue to operate. The inhaler should be discarded when the counter reads 000.

Keep out of reach of children. Avoid spraying in eyes.

Contents Under Pressure: Do not puncture. Do not use or store near heat or open flame. Exposure to temperatures above 120°F may cause bursting. Never throw into fire or incinerator.

Store at 25°C (77°F); excursions permitted from 15° to 30°C (59° to 86°F). Store the inhaler with the mouthpiece down. For best results, the inhaler should be at room temperature before use. SHAKE WELL BEFORE USING.

FLOVENT HFA does not contain CFCs as the propellant.

17 PATIENT COUNSELING INFORMATION

See FDA-approved patient labeling (Patient Information and Instructions for Use).

17.1 Oral Candidiasis

Patients should be advised that localized infections with Candida albicans have occurred in the mouth and pharynx in some patients. If oropharyngeal candidiasis develops, it should be treated with appropriate local or systemic (i.e., oral antifungal) therapy while still continuing therapy with FLOVENT HFA, but at times therapy with FLOVENT HFA may need to be temporarily interrupted under close medical supervision. Rinsing the mouth after inhalation is advised.

17.2 Status Asthmaticus and Acute Asthma Symptoms

Patients should be advised that FLOVENT HFA is not a bronchodilator and is not intended for use as rescue medication for acute asthma exacerbations. Acute asthma symptoms should be treated with an inhaled, short-acting beta2-agonist such as albuterol. Patients should be instructed to contact their physicians immediately if there is deterioration of their asthma.

17.3 Immunosuppression

Patients who are on immunosuppressant doses of corticosteroids should be warned to avoid exposure to chickenpox or measles and if they are exposed to consult their physicians without delay. Patients should be informed of potential worsening of existing tuberculosis, fungal, bacterial, viral, or parasitic infections, or ocular herpes simplex.

17.4 Hypercorticism and Adrenal Suppression

Patients should be advised that FLOVENT HFA may cause systemic corticosteroid effects of hypercorticism and adrenal suppression. Additionally, patients should be instructed that deaths due to adrenal insufficiency have occurred during and after transfer from systemic corticosteroids. Patients should taper slowly from systemic corticosteroids if transferring to FLOVENT HFA.

17.5 Hypersensitivity Reactions, Including Anaphylaxis

Patients should be advised that hypersensitivity reactions including anaphylaxis, angioedema, urticaria, and bronchospasm may occur after administration of FLOVENT HFA. Patients should discontinue FLOVENT HFA if such reactions occur.

17.6 Reduction in Bone Mineral Density

Patients who are at an increased risk for decreased BMD should be advised that the use of corticosteroids may pose an additional risk.

17.7 Reduced Growth Velocity

Patients should be informed that orally inhaled corticosteroids, including FLOVENT HFA, may cause a reduction in growth velocity when administered to pediatric patients. Physicians should closely follow the growth of children and adolescents taking corticosteroids by any route.

17.8 Ocular Effects

Long-term use of inhaled corticosteroids may increase the risk of some eye problems (cataracts or glaucoma); regular eye examinations should be considered.

17.9 Use Daily for Best Effect

Patients should use FLOVENT HFA at regular intervals as directed. Individual patients will experience a variable time to onset and degree of symptom relief and the full benefit may not be achieved until treatment has been administered for 1 to 2 weeks or longer. Patients should not increase the prescribed dosage but should contact their physicians if symptoms do not improve or if the condition worsens. Patients should be instructed not to stop use of FLOVENT HFA abruptly. Patients should contact their physicians immediately if they discontinue use of FLOVENT HFA.

DISKUS, FLOVENT, ROTADISK, and VENTOLIN are registered trademarks of GlaxoSmithKline.

AeroChamber Plus is a registered trademark and AeroChamber Z-STAT Plus is a trademark of Monaghan Medical Corp. or an affiliate of Monaghan Medical Corp.

GlaxoSmithKline

Research Triangle Park, NC 27709

©2012, GlaxoSmithKline. All rights reserved.

January 2012

FLH:4PI

Additional barcode labeling by:
Physicians Total Care, Inc.
Tulsa, Oklahoma 74146

PHARMACIST—DETACH HERE AND GIVE LEAFLET TO PATIENT

Patient Information

FLOVENT® [flō′ vent] HFA 44 mcg

(fluticasone propionate 44 mcg)

Inhalation Aerosol

FLOVENT® HFA 110 mcg

(fluticasone propionate 110 mcg)

Inhalation Aerosol

FLOVENT® HFA 220 mcg

(fluticasone propionate 220 mcg)

Inhalation Aerosol

FOR ORAL INHALATION ONLY

Read this leaflet carefully before you start to use FLOVENT HFA Inhalation Aerosol.

Keep this leaflet because it has important summary information about FLOVENT HFA. This leaflet does not contain all the information about your medicine. If you have any questions or are not sure about something, you should ask your doctor or pharmacist.

Read the new leaflet that comes with each refill of your prescription because there may be new information.

What is FLOVENT HFA?

FLOVENT HFA contains a medicine called fluticasone propionate, which is a synthetic corticosteroid. Corticosteroids are natural substances found in the body that help fight inflammation. Corticosteroids are used to treat asthma because they reduce airway inflammation.

FLOVENT HFA is used to treat asthma in patients 4 years and older. When inhaled regularly, FLOVENT HFA also helps to prevent symptoms of asthma.

FLOVENT HFA comes in 3 strengths. Your doctor has prescribed the one that is best for your condition.

Who should not use FLOVENT HFA?

Do not use FLOVENT HFA if you:

- are allergic to any of the ingredients in FLOVENT HFA or other inhaled corticosteroids. See “What are the ingredients in FLOVENT HFA?” below.
- have an acute asthma attack or status asthmaticus. FLOVENT HFA is not a bronchodilator and should not be used to give you fast relief from your breathing problems during an asthma attack. Always use a short-acting bronchodilator (rescue medicine), such as albuterol inhaler, during a sudden asthma attack. You must take FLOVENT HFA at regular times as recommended by your doctor, and not as an emergency medicine.

What should I tell my doctor before taking FLOVENT HFA?

Tell your doctor if you:

- have liver problems.
- have been exposed to chickenpox or measles.
- have any other medical conditions.
- are pregnant or planning to become pregnant. It is not known if FLOVENT HFA will harm your unborn baby.
- are breastfeeding a baby. It is not known if FLOVENT HFA passes into your breast milk.

Tell your doctor about all the medicines you take including prescription and non-prescription medicines, vitamins, and herbal supplements. FLOVENT HFA may affect the way other medicines work, and other medicines may affect how FLOVENT HFA works. Especially, tell your doctor if you take:

- a medicine containing ritonavir (commonly used to treat HIV infection or AIDS). The anti-HIV medicines NORVIR® (ritonavir capsules) Soft Gelatin, NORVIR (ritonavir oral solution), and KALETRA® (lopinavir/ritonavir) tablets contain ritonavir.
- any other corticosteroid medicines.
- ketoconazole (NIZORAL®), an antifungal medicine.

How should I use FLOVENT HFA?

1. It is important that you inhale each dose as your doctor has prescribed. The prescription label provided by your pharmacist will usually tell you what dose to take and how often. If it doesn’t or if you aren’t sure, ask your doctor or pharmacist. DO NOT inhale more doses or use your FLOVENT HFA more often than your doctor has prescribed.

2. It may take 1 to 2 weeks or longer for this medicine to work, and it is very important that you use it regularly. Do not stop taking FLOVENT HFA, even if you are feeling better, unless your doctor tells you to.

3. If you miss a dose, just take your next scheduled dose when it is due. Do not double the dose.

4. Your doctor may prescribe additional medicine (such as fast-acting bronchodilators) for emergency relief if a sudden asthma attack occurs. Contact your doctor if:

- an asthma attack does not respond to the additional medicine or
- you need more of the additional medicine than usual.

5. If you also use another medicine by inhalation, you should ask your doctor for instructions on when to use it while you are also using FLOVENT HFA.

6. Children should use FLOVENT HFA with an adult’s help, as instructed by the child’s healthcare provider. A valved holding chamber (a kind of spacer) and face mask may be used to deliver FLOVENT HFA to young patients.

What should I avoid while taking FLOVENT HFA?

If you have not had or not been vaccinated against chickenpox, measles, or active tuberculosis, you should stay away from people who are infected.

What are the possible side effects of FLOVENT HFA?

FLOVENT HFA can cause serious side effects, including:

- fungal infections (thrush) in your mouth and throat. Tell your doctor if you have any redness or white-colored coating in your mouth
- decreased ability to fight infections. Symptoms of infection may include: fever, pain, aches, chills, feeling tired, nausea and vomiting. Tell your doctor about any signs of infection while you use FLOVENT HFA.
- decreased adrenal function (adrenal insufficiency). Symptoms of decreased adrenal function include tiredness, weakness, nausea and vomiting, and low blood pressure. Decreased adrenal function can lead to death
- allergic reaction (anaphylaxis). Call your doctor and stop FLOVENT HFA right away if you have any symptoms of an allergic reaction:
- swelling of the face, throat and tongue
- hives
- rash
- breathing problems
- lower bone mineral density. This may be a problem for people who already have a higher chance of low bone density (osteoporosis).
- slow growth in children. The growth of children using FLOVENT HFA should be checked regularly.
- eye problems including glaucoma and cataracts. Tell your doctor about any vision changes while using FLOVENT HFA. Your doctor may tell you to have your eyes checked.
- increased wheezing (bronchospasm). Increased wheezing can happen right away after using FLOVENT HFA. Always have a rescue inhaler with you to treat sudden wheezing.

Tell your doctor right away if you have any of the serious side effects listed above or if you have worsening lung symptoms.

The most common side effects of FLOVENT HFA include:

- a cold or upper respiratory tract infection
- throat irritation
- headache
- fever
- diarrhea
- ear infection

Tell your doctor if you have any side effects that bother you or that do not go away. These are not all the possible side effects of FLOVENT HFA. For more information ask your doctor or pharmacist.

Call your doctor for medical advice about side effects. You may report side effects to FDA at 1-800-FDA-1088 or 1-800-332-1088.

How should I store FLOVENT HFA?

Store FLOVENT HFA at room temperature between 59°and 86°F (15°-30°C). Store the inhaler with the mouthpiece down. For best results, the inhaler should be at room temperature before use.

Keep FLOVENT HFA and all medicines out of the reach of children.

This Patient Information leaflet summarizes the most important information about FLOVENT HFA. If you would like more information, talk with your healthcare provider. You can ask your pharmacist or doctor for information about FLOVENT HFA that is written for health professionals. You can also contact the company that makes FLOVENT HFA (toll free) at 1-888-825-5249.

What are the ingredients in FLOVENT HFA?

Active ingredient: fluticasone propionate (micronized)

Inactive ingredient: propellant HFA-134a

Instructions for Using FLOVENT HFA

The parts of your FLOVENT HFA

There are 2 main parts to your FLOVENT HFA inhaler—the metal canister that holds the medicine and the dark orange plastic actuator that sprays the medicine from the canister (see Figure 1).

Figure 1

The canister has a counter to show how many sprays of medicine you have left. The number shows through a window in the back of the actuator. The counter starts at 124. The number will count down by 1 each time you spray the inhaler. The counter will stop counting at 000.

Never try to change the numbers or take the counter off the metal canister. The counter cannot be reset, and it is permanently attached to the canister.

The mouthpiece of the actuator is covered by a cap. A strap on this cap keeps it attached to the actuator.

Do not use the actuator with a canister of medicine from any other inhaler. And do not use a FLOVENT HFA canister with an actuator from any other inhaler.

Using your FLOVENT HFA

- The inhaler should be at room temperature before you use it.
- Take your FLOVENT HFA inhaler out of the moisture-protective foil pouch just before you use it for the first time. Safely throw away the foil pouch and the drying packet that comes inside the pouch.
- Priming the inhaler:
  Before you use FLOVENT HFA for the first time, you must prime the inhaler so that you will get the right amount of medicine when you use it. To prime the inhaler, take the cap off the mouthpiece and shake the inhaler well for 5 seconds. Then spray the inhaler into the air away from your face. Avoid spraying in eyes. Shake and spray the inhaler like this 3 more times to finish priming it. The counter should now read 120.
  You must prime the inhaler again if you have not used it in more than 7 days or if you drop it. Take the cap off the mouthpiece and shake the inhaler well for 5 seconds. Then spray it 1 time into the air away from your face.
- If a child needs help using the inhaler, an adult should help the child use the inhaler with or without a valved holding chamber, which may also be attached to a face mask. The adult should follow the instructions that came with the valved holding chamber. An adult should watch a child use the inhaler to be sure it is used correctly.

Read the following 7 steps before using FLOVENT HFA and follow them at each use. If you have any questions, ask your doctor or pharmacist.

Figure 2

1. Take the cap off the mouthpiece of the actuator (see Figure 2). Look inside the mouthpiece for foreign objects, and take out any you see.
  Make sure the canister fits firmly in the actuator.
  Shake the inhaler well for 5 seconds.
2. Hold the inhaler with the mouthpiece down (see Figure 2). Breathe out through your mouth and push as much air from your lungs as you can. Put the mouthpiece in your mouth and close your lips around it.
3. Push the top of the canister all the way down while you breathe in deeply and slowly through your mouth (see Figure 3).
  Right after the spray comes out, take your finger off the canister. After you have breathed in all the way, take the inhaler out of your mouth and close your mouth.
4. Hold your breath as long as you can, up to 10 seconds. Then breathe normally.
5. Wait about 30 seconds and shake the inhaler well for 5 seconds. Repeat steps 2 through 4.
6. After you finish taking this medicine, rinse your mouth with water. Spit out the water. Do not swallow it.
7. Put the cap back on the mouthpiece after each time you use the inhaler. Make sure it snaps firmly into place.

Figure 3

Cleaning your FLOVENT HFA

Clean the inhaler at least once a week after your evening dose. It is important to keep the canister and plastic actuator clean so the medicine will not build-up and block the spray.

Figure 4

1. Take the cap off the mouthpiece. The strap on the cap will stay attached to the actuator. Do not take the canister out of the plastic actuator.
2. Use a clean cotton swab dampened with water to clean the small circular opening where the medicine sprays out of the canister. Gently twist the swab in a circular motion to take off any medicine (see Figure 4). Repeat with a new swab dampened with water to take off any medicine still at the opening.
3. Wipe the inside of the mouthpiece with a clean tissue dampened with water. Let the actuator air-dry overnight.
4. Put the cap back on the mouthpiece after the actuator has dried.

Replacing your FLOVENT HFA

- When the counter reads 020, you should refill your prescription or ask your doctor if you need a refill of your prescription.
- When the counter reads 000, throw the inhaler away. You should not keep using the inhaler because you will not receive the right amount of medicine.
- Do not use the inhaler after the expiration date, which is on the packaging it comes in.

FLOVENT is a registered trademark of GlaxoSmithKline.

The other brands listed are trademarks of their respective owners and are not trademarks of GlaxoSmithKline. The makers of these brands are not affiliated with and do not endorse GlaxoSmithKline or its products.

GlaxoSmithKline

Research Triangle Park, NC 27709

©2010, GlaxoSmithKline. All rights reserved.

November 2010

FLH:2PIL

PACKAGE LABEL

Principal Display Panel

NDC 54868-5995-0

Flovent® HFA 44 mcg

(fluticasone propionate 44 mcg) Inhalation Aerosol

With Dose Counter

Rx only

FOR ORAL INHALATION ONLY

Contents: Each canister contains a microcrystalline suspension of fluticasone propionate (micronized) in propellant HFA-134a (1,1,1,2-tetrafluoroethane).

Each actuation of the inhaler delivers 50 mcg of fluticasone propionate from the valve and 44 mcg from the actuator.

IMPORTANT: Read accompanying Patient Information leaflet carefully for further information.

Dosage: Use only as directed by your doctor.

Store at 25oC (77oF); excursions permitted to 15o-30oC (59o-86oF).

Net Wt. 10.6g 120 Metered Actuations

PACKAGE LABEL

Principal Display Panel

NDC 54868-5362-0

Flovent® HFA 110 mcg

(fluticasone propionate 110 mcg) Inhalation Aerosol

With Dose Counter

Rx only

FOR ORAL INHALATION ONLY

Contents: Each canister contains a microcrystalline suspension of fluticasone propionate (micronized) in propellant HFA-134a (1,1,1,2-tetrafluoroethane).

Each actuation of the inhaler delivers 125 mcg of fluticasone propionate from the valve and 110 mcg from the actuator.

IMPORTANT: Read accompanying Patient Information leaflet carefully for further information.

Dosage: Use only as directed by your doctor.

Store at 25oC (77oF); excursions permitted to 15o-30oC (59o-86oF).

Net Wt. 12g 120 Metered Actuations

PACKAGE LABEL

Principal Display Panel

NDC 54868-5637-0

Flovent® HFA 220 mcg

(fluticasone propionate 220 mcg) Inhalation Aerosol

With Dose Counter

Rx only

FOR ORAL INHALATION ONLY

Contents: Each canister contains a microcrystalline suspension of fluticasone propionate (micronized) in propellant HFA-134a (1,1,1,2-tetrafluoroethane).

Each actuation of the inhaler delivers 250 mcg of fluticasone propionate from the valve and 220 mcg from the actuator.

IMPORTANT: Read accompanying Patient Information leaflet carefully for further information.

Dosage: Use only as directed by your doctor.

Store at 25oC (77oF); excursions permitted to 15o-30oC (59o-86oF).

Net Wt. 12g 120 Metered Actuations